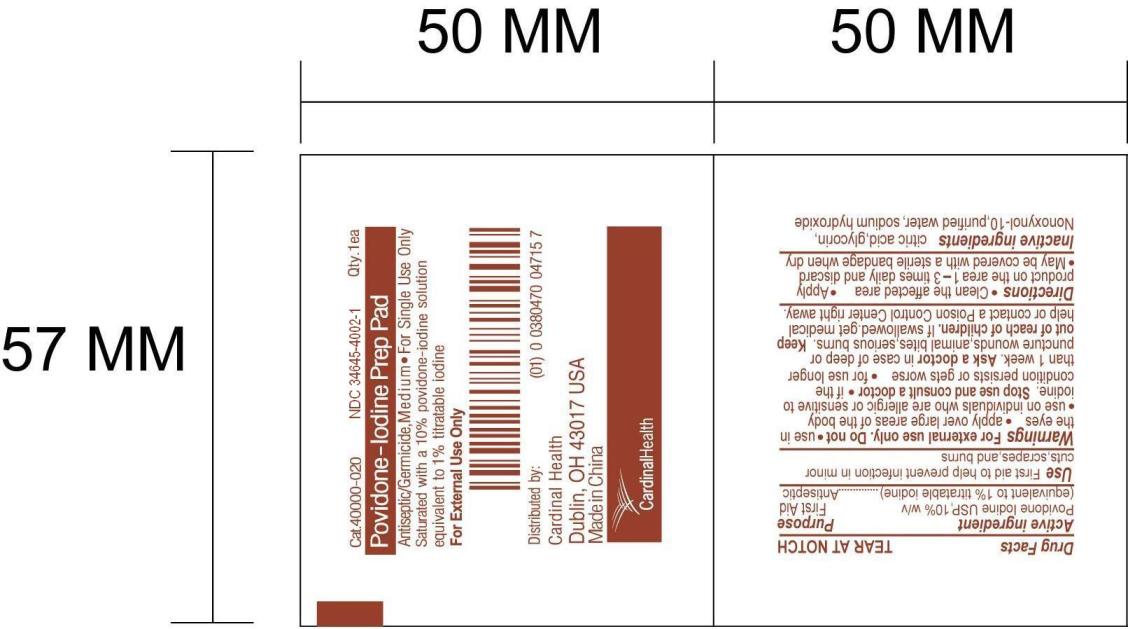 DRUG LABEL: Povidone-Iodine Prep Pad
NDC: 34645-4002 | Form: SWAB
Manufacturer: Jiangsu Province JianErKang Medical Dressing Co. ,Ltd.
Category: otc | Type: HUMAN OTC DRUG LABEL
Date: 20100101

ACTIVE INGREDIENTS: POVIDONE-IODINE 0.1 mL/1 mL

Drug Facts

PACKAGE LABEL

Cat.40000-020 NDC 34645-4002-1 Qty. 1ea

Povidone-Iodine Prep Pad

Antiseptic/Germicide, Medium*For Single Use Only

Saturated with a 10% povidone-iodine solution

equivalent to 1% titratable iodine

For External Use Only

Distributed by:

Cardinal Health

Dublin, OH 43017 USA

Made in China

Active ingredient

Povidone Iodine USP, 10% w/v

(equivalent to 1% titratable iodine)

Purpose

First Aid

Antiseptic

Use

First aid to help prevent infection in minor cuts, scrapes, and burns

Warnings

For external use only.

Do not * use in the eyes * apply over large areas of the body

* use on individuals who are allergic or sensitive to iodine

Stop use and consult a doctor

if the condition persists or gets worse

for use longer than 1 week

Ask doctor

in case of deep or puncture wounds, animal bites, serious burns.

Keep out of reach of children.

If swallowed, get medical help or contact Poison Control Center right away.

Directions

Clean the affected area

Apply product on the area 1-3 times daily and discard

May be covered with a sterile bandage when dry

Inactive ingredients

ctric acid, glycerin, Nonoxynol-10, purified water, sodium hydroxide

Image of Pouch Label